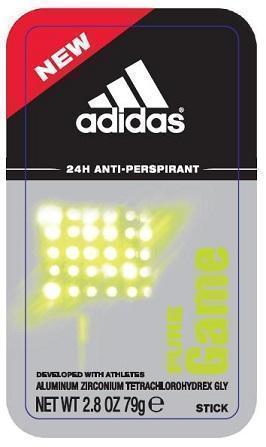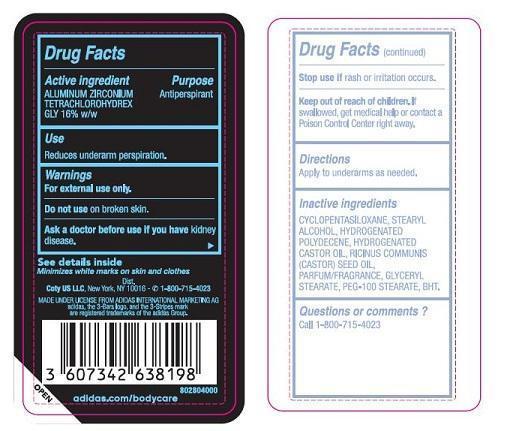 DRUG LABEL: Adidas 24H Anti Perspirant
NDC: 66184-143 | Form: Stick
Manufacturer: Coty US LLC
Category: otc | Type: HUMAN OTC DRUG LABEL
Date: 20121011

ACTIVE INGREDIENTS: ALUMINUM ZIRCONIUM TETRACHLOROHYDREX GLY 12.6 g/79 g
INACTIVE INGREDIENTS: STEARYL ALCOHOL; HYDROGENATED POLYDECENE (550 MW); HYDROGENATED CASTOR OIL; RICINUS COMMUNIS SEED; GLYCERYL STEARATE SE; PEG-100 STEARATE; CYCLOMETHICONE 5

ACTIVE INGREDIENT

Aluminum Zirconium Tetrachlorohydrex GLY 16% w/w

PURPOSE

Antiperspirant

Keep out of reach of children. If swallowed, get medical help or contact a Poison Control Center right away.

INDICATIONS AND USAGE

Reduces underarm perspiration.

Apply to underarms as needed.

WARNINGS

For external use only.

Do not use on broken skin.

Ask a doctor before use if you have kidney disease.

DOSAGE AND ADMINISTRATION

Aluminum Zirconium Tetrachlorohydrex

GLY 16% w/w

INACTIVE INGREDIENT

Cyclopentasiloxane, Stearyl Alcohol, Hydrogenated Polydecene, Hydrogenated Castor Oil, Ricinus Communis (Castor) Seed Oil, Parfum/Fragrance, Glyceryl Stearate, PEG-100 Stearate, BHT.